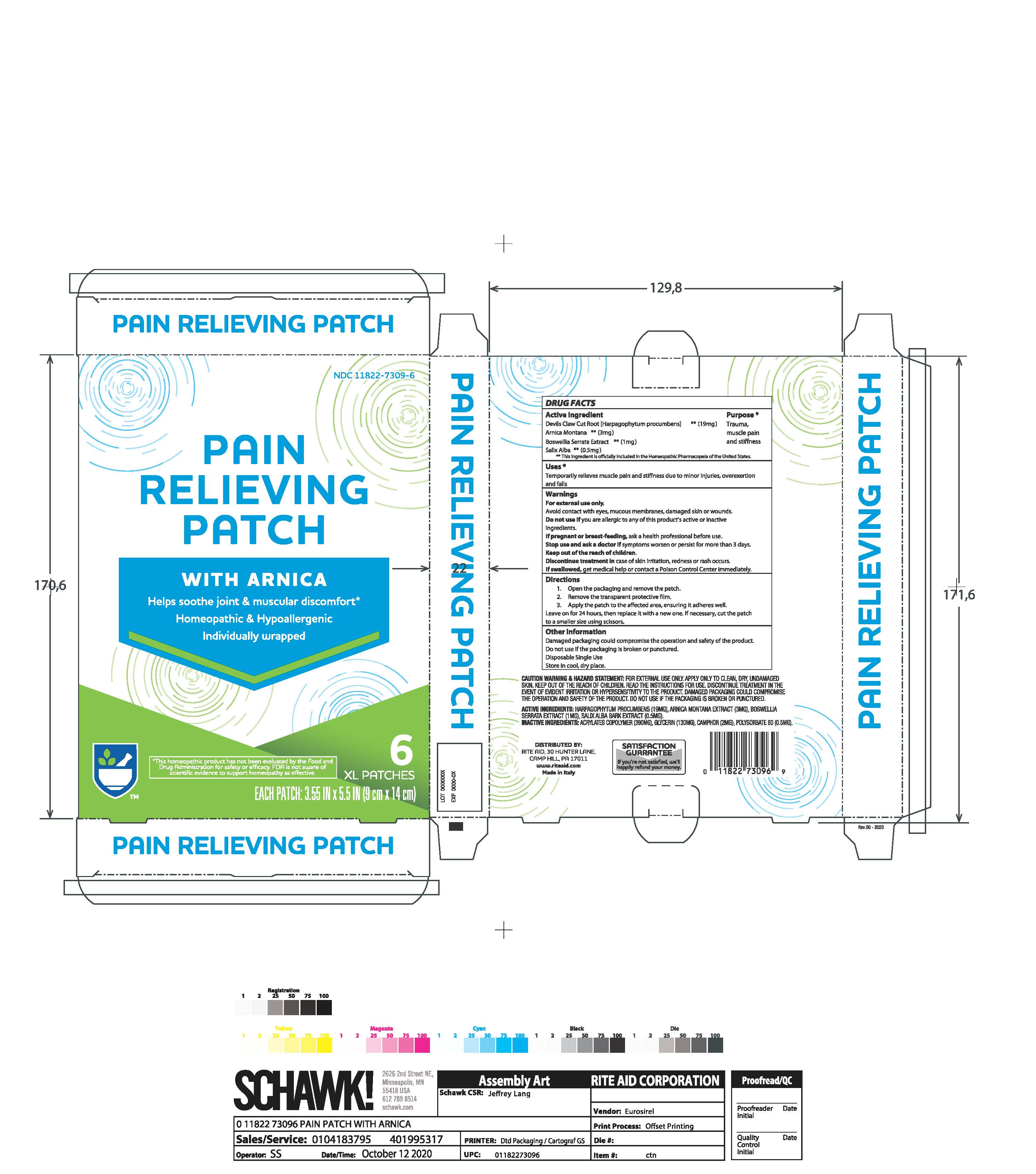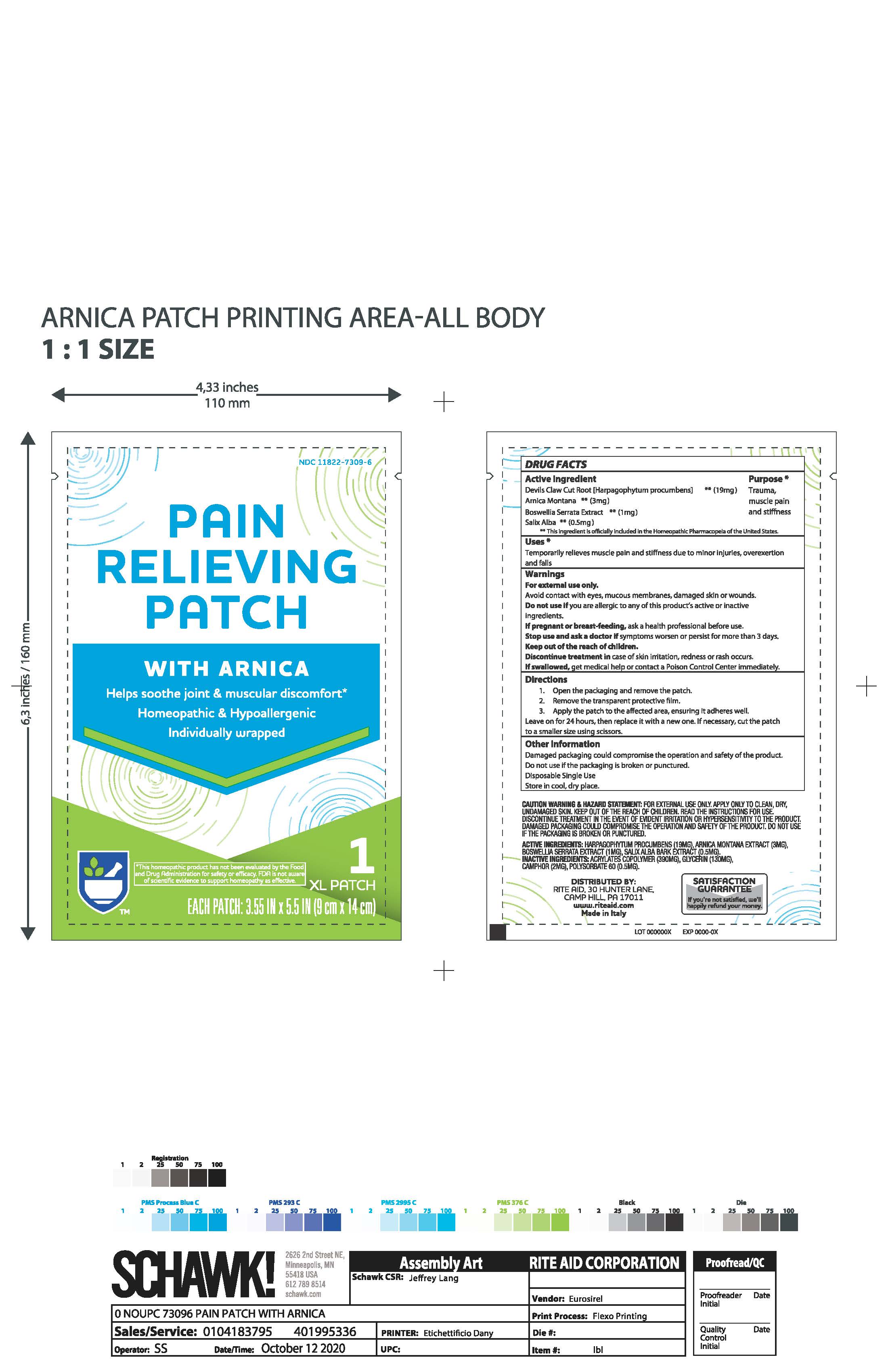 DRUG LABEL: Rite Aid Pain Relieving XL Patch With Arnica
NDC: 11822-7309 | Form: PATCH
Manufacturer: Rite Aid
Category: homeopathic | Type: HUMAN OTC DRUG LABEL
Date: 20201021

ACTIVE INGREDIENTS: SALIX ALBA BARK 0.5 mg/1 1; BOSWELLIA SERRATA RESIN OIL 1 mg/1 1; HARPAGOPHYTUM PROCUMBENS ROOT 19 mg/1 1; ARNICA MONTANA 3 mg/1 1
INACTIVE INGREDIENTS: GLYCERIN; POLYSORBATE 60; BUTYL ACRYLATE/METHYL METHACRYLATE/METHACRYLIC ACID COPOLYMER (18000 MW); CAMPHOR (NATURAL)

Rite Aid Pain Relieving XL Patch With Arnica

ACTIVE INGREDIENT

Devil's Claw Cut Root [Harpagophytum procumbens] 19mg

Arnica Montana 3mg

Boswellia Serrata Extract 1mg

Salix Alba 0.5mg

INACTIVE INGREDIENT

Acrylates Copolymer (390mg), Glycerin (130mg), Camphor (2mg), Polysorbate 60 (0.5mg)

DOSAGE AND ADMINISTRATION

1. Open the packaging and remove the patch.
2. Remove the transparent protective film.
3. Apply the patch to the affected area, ensuring it adheres well. Leave on for 24 hours, then replace it with a new one. If necessary, cut the patch to a smaller size using scissors.

INDICATIONS AND USAGE

Temporarily relieves muscle pain and stiffness due to minor injuries, overexcertion and falls

WARNINGS

For external use only.

Avoid contact with eyes, mucous membranes, damaged skin, or wounds.

Do not useif you are allergic to any of this product's active or inactive ingredients.

If pregnant or breast-feeding, ask a health professional before use.

Stop use and ask a doctorif symptoms worsen or persist for more than 3 days.

Discontinue treatment in case of skin irritation, redness or rash occurs.

If swallowed, get medical help or contact a Poison Control Center immediately.

Keep out of reach of children.

OTHER SAFETY INFORMATION

Damaged packaging could compromise the operation and safety of the product.

Do not use if the packaging is broken or punctured.

Disposable Single Use

Store in cool, dry place.

PURPOSE

Temporary relief of trauma, muscle pain and stiffness